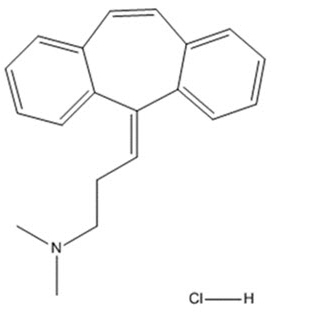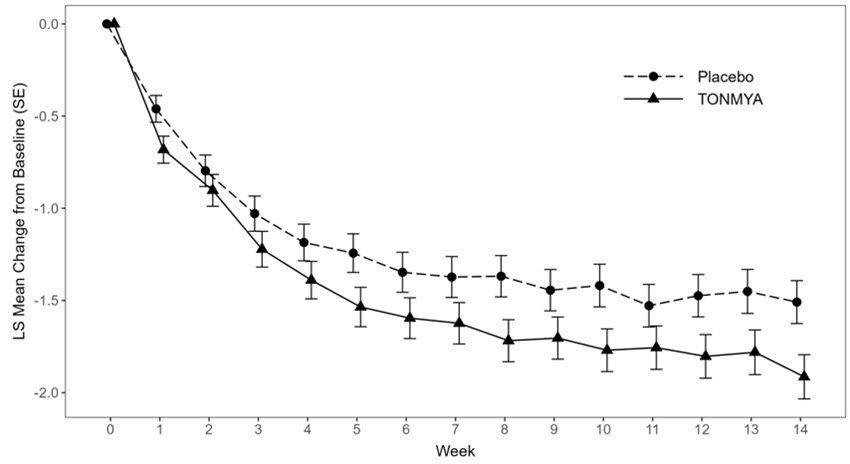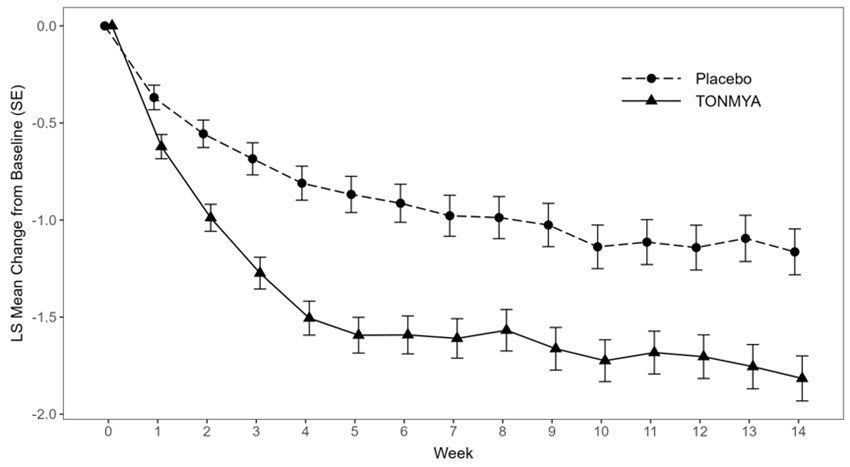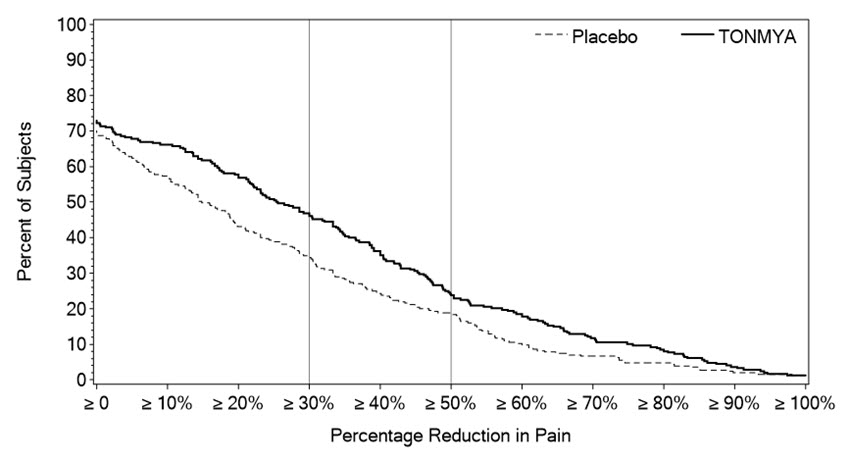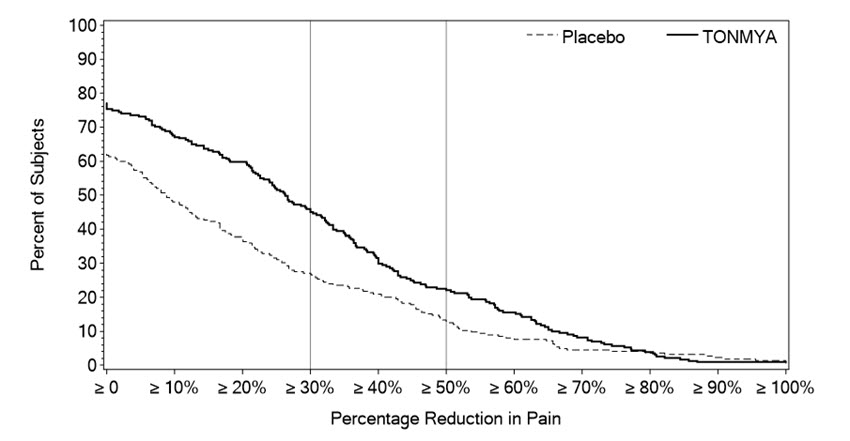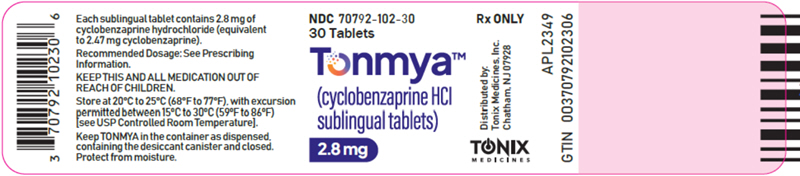 DRUG LABEL: TONMYA
NDC: 70792-102 | Form: TABLET, ORALLY DISINTEGRATING
Manufacturer: Tonix Medicines, Inc.
Category: prescription | Type: HUMAN PRESCRIPTION DRUG LABEL
Date: 20251023

ACTIVE INGREDIENTS: Cyclobenzaprine Hydrochloride 2.8 mg/1 1
INACTIVE INGREDIENTS: Mannitol; Starch, Corn; CROSPOVIDONE (120 .MU.M); DIBASIC POTASSIUM PHOSPHATE; SODIUM STEARYL FUMARATE; SILICON DIOXIDE; D&C YELLOW NO. 10

HIGHLIGHTS OF PRESCRIBING INFORMATION

These highlights do not include all the information needed to use TONMYA safely and effectively. See full prescribing information for TONMYA.
TONMYA™ (cyclobenzaprine hydrochloride sublingual tablets)
Initial U.S. Approval: 1977

1 INDICATIONS AND USAGE

TONMYA is indicated for the treatment of fibromyalgia in adults (1).

2 DOSAGE AND ADMINISTRATION

- Recommended dosage of TONMYA is 5.6 mg administered sublingually once daily at bedtime (2.1):
  - Starting dose: Days 1 to 14, administer 2.8 mg (1 sublingual tablet) once daily at bedtime.
  - Target dose: Days 15 and thereafter, administer 5.6 mg (2 sublingual tablets) once daily at bedtime.
  - Maximum recommended dosage: 5.6 mg once daily.
- Ensure mouth is moist with sips of water before sublingual administration (2.4, 5.6, 6.1)
- Do not swallow whole, cut, crush, or chew (2.4)
- Geriatric patients: Recommended dosage is 2.8 mg administered sublingually once daily at bedtime (2.2, 8.5)
- Hepatic impairment (HI): Recommended dosage in patients with mild HI is 2.8 mg administered sublingually once daily at bedtime. Use not recommended in patients with moderate HI or severe HI (2.3, 8.6).
- See important administration instructions in the Full Prescribing Information (2.4, 2.5, 2.6).

3 DOSAGE FORMS AND STRENGTHS

Sublingual tablets: 2.8 mg of cyclobenzaprine hydrochloride (3).

4 CONTRAINDICATIONS

- Hypersensitivity to cyclobenzaprine or any inactive ingredient in TONMYA (4)
- Concomitant use of monoamine oxidase (MAO) inhibitors or within 14 days after their discontinuation (4)
- During acute recovery phase of myocardial infarction and in patients with arrhythmias, heart block or conduction disturbances, or congestive heart failure (4)
- Hyperthyroidism (4)

5 WARNINGS AND PRECAUTIONS

- Embryofetal Toxicity: Based on animal data, TONMYA may cause neural tube defects when used two weeks prior to conception and through the first trimester of pregnancy. Advise females of reproductive potential of the potential risk and to use effective contraception during treatment and for two weeks after the final dose. (5.1, 8.1, 8.3)
- Serotonin Syndrome: Potentially life-threatening serotonin syndrome has been reported with cyclobenzaprine when used in combination with other drugs. Immediately discontinue concomitant treatment with TONMYA and a serotonergic agent if serotonin syndrome symptoms occur and initiate supportive symptomatic treatment. If concomitant treatment with TONMYA and other serotonergic drugs is clinically warranted, careful observation is advised, particularly during treatment initiation or dosage increases. (5.2)
- Tricyclic Antidepressant-like Adverse Reactions: TCAs have been reported to produce arrhythmias, sinus tachycardia, prolongation of the conduction time leading to myocardial infarction and stroke. TCAs lower the seizure threshold, and are associated with serious CNS reactions. If clinically significant CNS symptoms develop, consider discontinuation of TONMYA. (5.3)
- Atropine-like Adverse Reactions: Use with caution in patients with a history of urinary retention, angle-closure glaucoma, increased intraocular pressure and in patients taking anticholinergic medications. (5.4)
- CNS Depression and Risk of Operating a Motor Vehicle or Hazardous Machinery: TONMYA monotherapy may cause CNS depression. Advise patients not to operate a motor vehicle or other dangerous machinery until they are reasonably certain that TONMYA therapy will not adversely affect their ability to engage in such activities. (5.5)
- Oral Mucosal Adverse Reactions: In clinical studies, oral mucosal adverse reactions occurred more frequently in TONMYA-treated patients compared to placebo-treated patients. Advise patients to moisten the mouth with sips of water before administration of TONMYA to reduce the risk of oral sensory changes (hypoesthesia). Consider discontinuation of TONMYA if severe reactions occur. (5.6)

6 ADVERSE REACTIONS

Most common adverse reactions (incidence ≥2% and at a higher incidence in TONMYA-treated patients compared to placebo-treated patients): oral hypoesthesia, oral discomfort, abnormal product taste, somnolence, oral paresthesia, oral pain, fatigue, dry mouth, and aphthous ulcer (6.1).

To report SUSPECTED ADVERSE REACTIONS, contact Tonix Medicines, Inc. at 1-888-869-7633 (1-888-TNXPMED) or FDA at 1-800-FDA-1088 or www.fda.gov/medwatch.

7 DRUG INTERACTIONS

- MAO Inhibitors: Life-threatening interactions may occur (4, 7)
- Other serotonergic Drugs: Serotonin syndrome has been reported (5.2, 7)
- CNS Depressants: CNS depressant effects of alcohol, barbiturates, and other CNS depressants may be enhanced (5.5, 7)
- Tramadol: Seizure risk may be enhanced (7)
- Guanethidine: Antihypertensive effect may be blocked (7)

8 USE IN SPECIFIC POPULATIONS

Hepatic impairment: The use of TONMYA is not recommended in patients with moderate HI (Child Pugh B) or severe HI (Child Pugh C) (2.3, 8.6).

FULL PRESCRIBING INFORMATION

1 INDICATIONS AND USAGE

TONMYA™ is indicated for treatment of fibromyalgia in adults.

2 DOSAGE AND ADMINISTRATION

2.1 Recommended Dosage

The recommended dosage of TONMYA is 5.6 mg administered sublingually once daily at bedtime:

- Starting dose: Days 1 to 14, administer 2.8 mg (1 sublingual tablet) once daily at bedtime.
- Target dose: Days 15 and thereafter, administer 5.6 mg (2 sublingual tablets) once daily at bedtime.
- Maximum recommended dosage: 5.6 mg once daily.

2.2 Recommended Dosage in Geriatric Patients

The recommended TONMYA dosage―and the maximum recommended dosage―in geriatric patients is 2.8 mg administered sublingually once daily at bedtime [see Use in Specific Populations (8.5)].

2.3 Recommended Dosage in Patients with Hepatic Impairment

The recommended TONMYA dosage―and the maximum recommended dosage―in patients with mild hepatic impairment is 2.8 mg administered sublingually once daily at bedtime. TONMYA is not recommended in patients with moderate or severe hepatic impairment [see Use in Specific Populations (8.6)].

2.4 Administration Instructions

TONMYA is only for sublingual use.

- Administer after brushing teeth and finishing other oral care and ensure a moist mouth/sublingual area by drinking a few sips of water prior to administration.
- Place the sublingual tablet(s) under the tongue until dissolved.
- Do not swallow whole, cut, crush, or chew.
- Avoid eating or drinking for at least 15 minutes after the sublingual tablet(s) has/have completely dissolved at bedtime and preferably avoid any hot, cold, or acidic beverages until the morning.
- Avoid talking for at least 5 minutes after administration.

2.5 Recommendations Regarding Missed Dose(s)

If you missed a TONMYA bedtime dose, take TONMYA the next evening. Do not take a missed dose during the day.

2.6 Pregnancy Testing Prior to Administration

Pregnancy testing is recommended in females of reproductive potential prior to initiating treatment with TONMYA [see Warnings and Precautions (5.1), and Use in Specific Populations (8.1, 8.3)]

3 DOSAGE FORMS AND STRENGTHS

Sublingual tablets: 2.8 mg of cyclobenzaprine hydrochloride - yellow and round with the letter "T" debossed on one face.

4 CONTRAINDICATIONS

- Hypersensitivity to cyclobenzaprine or any inactive ingredient in TONMYA. Hypersensitivity reactions may manifest as an anaphylactic reaction, urticaria, facial and/or tongue swelling, or pruritus. Discontinue TONMYA if a hypersensitivity reaction is suspected.
- Concomitant use of monoamine oxidase (MAO) inhibitors or within 14 days after discontinuation of a MAO inhibitor. Hyperpyretic crisis seizures and deaths have occurred in patients who received cyclobenzaprine (or structurally similar tricyclic antidepressants) concomitantly with MAO inhibitors drugs.
- During the acute recovery phase of myocardial infarction, and in patients with arrhythmias, heart block or conduction disturbances, or congestive heart failure.
- Hyperthyroidism.

5 WARNINGS AND PRECAUTIONS

5.1 Embryofetal Toxicity

Based on data from animal reproduction studies, TONMYA may cause an increased risk of neural tube defects when administered to a pregnant female two weeks prior to conception and during the first trimester of pregnancy. Neural tube defects (splayed vertebral arches and spina bifida occulta) were observed in a rabbit embryofetal development study at the highest maternal dose tested, in the absence of maternal toxicity. Because neural tube development occurs early in pregnancy, often before pregnancy is recognized, advise females of reproductive potential of the potential risk to the fetus and avoid use of TONMYA two weeks prior to conception and through the first trimester of pregnancy.

Perform a pregnancy test prior to initiation of treatment with TONMYA to exclude use of TONMYA during the first trimester of pregnancy.

Advise females of reproductive potential to use effective contraception during TONMYA treatment and for two weeks after the final dose [see Use in Specific Populations (8.1, 8.3)].

5.2 Serotonin Syndrome

The development of a potentially life-threatening serotonin syndrome has been reported with cyclobenzaprine when used in combination with other drugs, such as selective serotonin reuptake inhibitors (SSRIs), serotonin norepinephrine reuptake inhibitors (SNRIs), tricyclic antidepressants (TCAs), tramadol, bupropion, meperidine, verapamil, or MAO inhibitors. The concomitant use of TONMYA with MAO inhibitors is contraindicated [see Contraindications (4)].

Serotonin syndrome symptoms may include mental status changes (e.g., confusion, agitation, hallucinations), autonomic instability (e.g., diaphoresis, tachycardia, labile blood pressure, hyperthermia), neuromuscular abnormalities (e.g., tremor, ataxia, hyperreflexia, clonus, muscle rigidity), and/or gastrointestinal symptoms (e.g., nausea, vomiting, diarrhea).

Treatment with TONMYA and any concomitant serotonergic agents should be discontinued immediately if serotonin syndrome symptoms occur and supportive symptomatic treatment should be initiated. If concomitant treatment with TONMYA and other serotonergic drugs is clinically warranted, careful observation is advised, particularly during treatment initiation or dosage increases.

5.3 Tricyclic Antidepressant-like Adverse Reactions

Cyclobenzaprine is structurally related to tricyclic antidepressants (TCAs).

TCAs have been reported to produce arrhythmias, sinus tachycardia, prolongation of the conduction time leading to myocardial infarction and stroke [see Contraindications (4)].

Some of the more TCA-associated serious central nervous system (CNS) reactions have occurred in short-term studies of oral cyclobenzaprine. If clinically significant CNS symptoms develop, consider discontinuation of TONMYA.

Caution should be used when TCAs are given to patients with a history of seizure disorder, because TCAs may lower the seizure threshold. Patients with a history of seizures should be monitored during TCA use to identify recurrence of seizures or increase in frequency of seizures.

5.4 Atropine-like Adverse Reactions

Because of its atropine-like action, TONMYA should be used with caution in patients with a history of urinary retention, angle-closure glaucoma, increased intraocular pressure, and in patients taking anticholinergic drugs.

5.5 CNS Depression and Risk of Operating a Motor Vehicle or Hazardous Machinery

TONMYA monotherapy may cause CNS depression and concomitant use of TONMYA with alcohol, barbiturates, or other CNS depressants may increase the risk of CNS depression [see Drug Interactions (7)].

Symptoms of CNS depression include somnolence. Advise patients not to operate a motor vehicle or dangerous machinery until they are reasonably certain that TONMYA therapy will not adversely affect their ability to engage in such activities.

5.6 Oral Mucosal Adverse Reactions

Oral mucosal adverse reactions, including sensory changes (e.g., numbness, tingling), discomfort, pain, irritation, inflammation, and lesions, occurred more frequently in patients treated with TONMYA compared to placebo (43% vs. 8%) [see Adverse Reactions (6.1)]. Reactions typically occurred within minutes of administration and most resolved within 60 minutes.

Five patients experienced severe oral mucosal adverse reactions, including sensory changes (paresthesia, hypoesthesia), inflammation (glossitis), oral pain, and dry mouth. Most severe oral mucosal adverse reactions resolved within days after TONMYA was discontinued and no treatment was required.

Advise patients to moisten the mouth with sips of water before administration of TONMYA to reduce the risk of oral sensory changes (hypoesthesia). Advise patients to report severe oral mucosal adverse reactions to their healthcare provider. Consider discontinuation of TONMYA if severe reactions occur.

6 ADVERSE REACTIONS

The following clinically significant reactions are described in greater detail, in other sections of this labeling:

- Embryofetal Toxicity [see Warnings and Precautions (5.1)]
- Serotonin Syndrome [see Warnings and Precautions (5.2)]
- Tricyclic Antidepressant-like Adverse Reactions [see Warnings and Precautions (5.3)]
- Atropine-like Adverse Reactions [see Warnings and Precautions (5.4)]
- CNS Depression [see Warnings and Precautions (5.5)]
- Oral Mucosal Adverse Reactions [see Warnings and Precautions (5.6)]

6.1 Clinical Trials Experience

Because clinical trials are conducted under widely varying conditions, adverse reaction rates observed in the clinical trials of a drug cannot be directly compared to rates in the clinical trials of another drug and may not reflect the rates observed in practice.

The safety of sublingual TONMYA (14 days of 2.8 mg once daily and then 5.6 mg once daily thereafter) is supported by three double-blind, placebo-controlled clinical trials (Trials 1, 2, and 3) in adult patients with fibromyalgia [see Clinical Studies (14)]. A total of 1,182 patients completed at least 14 weeks of daily treatment, including 580 TONMYA-treated patients (14 days of 2.8 mg once daily and then 5.6 mg once daily thereafter) and 602 placebo-treated patients.

Table 1 summarizes the most common adverse reactions in Trials 1, 2, and 3 (≥2% of TONMYA-treated patients and at a higher incidence in TONMYA-treated patients compared to placebo-treated patients).

Table 1: Adverse Reactions Reported in ≥2% of TONMYA-Treated Patients and a Higher Incidence than Placebo-Treated Patients in Adult Patients with Fibromyalgia (Trials 1, 2, and 3)
Adverse Reactions | Placebo (N = 739) | TONMYA (N = 735)
Oral hypoesthesia [Oral hypoesthesia includes hypoesthesia and teeth hypoesthesia] | 0.7% | 23%
Oral discomfort [Oral discomfort includes tongue discomfort] | 0.7% | 9%
Abnormal product taste | 0.7% | 9%
Somnolence [Somnolence includes hypersomnia, lethargy, and sedation] | 2% | 6%
Oral paresthesia [Oral paresthesia includes paresthesia and teeth hyperesthesia] | 0.4% | 6%
Oral pain [Oral pain includes glossodynia] | 1% | 5%
Fatigue [Fatigue includes asthenia and lethargy] | 2% | 4%
Dry mouth [Dry mouth includes dry throat] | 2% | 3%
Aphthous ulcer | 0.5% | 2%

Oral Mucosal Adverse Reactions in Trials 1, 2, and 3

In Trials 1, 2, and 3, 43% of TONMYA-treated patients compared to 8% of placebo-treated patients experienced at least 1 treatment-emergent oral mucosal adverse reaction. The most common oral mucosal adverse reactions included oral hypoesthesia, abnormal product taste, oral paresthesia, tongue discomfort, oral discomfort, glossodynia, oral pain, and aphthous ulcer. The majority (82%) of oral mucosal adverse reactions began within minutes of dosing, and of those, 88% occurred after nearly every dose. Almost two-thirds lasted less than 60 minutes. Of the approximately one-third that lasted longer than 60 minutes, 63% were present the next morning.

Five patients (0.7% of TONMYA-treated patients) experienced severe oral mucosal adverse reactions, including paresthesia, glossitis, hypoesthesia, oral pain, and dry mouth. Most reactions resolved within days after TONMYA was discontinued. Oral mucosal adverse reactions leading to discontinuation occurred more frequently in TONMYA-treated patients compared to placebo-treated patients (4.5% vs. 0.5%).

Adverse Reactions from Other Trials

In an open-label, long-term 40 to 52-week safety trial (Trial 4) in an unapproved population of patients previously exposed to 5.6 mg TONMYA once daily (maximum recommended dosage) or placebo, 56 patients were treated with 5.6 mg of TONMYA for at least 1 year. The most common adverse reactions in the TONMYA-treated patients (>5%) were oral hypoesthesia (45%), somnolence (18%), abnormal product taste (7%), and paresthesia oral (7%).

In an open-label, long-term 52 week safety trial of adult patients with fibromyalgia previously been exposed to 2.8 mg TONMYA once daily (one half the recommended dosage [see Dosage and Administration (2.1)]) or placebo (Trial 5), 97 patients were treated for at least 1 year with 2.8 mg of TONMYA once daily. The most common adverse reactions (>5%) in the TONMYA-treated patients were hypoesthesia oral (15%), fatigue (7%), sinusitis (7%), and abnormal product taste (6%).

6.2 Postmarketing Experience

The following adverse reactions have been reported in clinical studies or postmarketing experience with cyclobenzaprine immediate-release (IR) products, cyclobenzaprine extended-release (ER) products, or TCAs. Because some of these reactions are reported voluntarily from a population of uncertain size, it is not always possible to reliably estimate their frequency or establish a causal relationship to drug exposure.

In a postmarketing surveillance program of cyclobenzaprine IR products, the adverse reactions reported most frequently were drowsiness, dry mouth, and dizziness, and adverse reactions reported in 1% to 3% of the patients were: fatigue/tiredness, asthenia, nausea, constipation, dyspepsia, unpleasant taste, blurred vision, headache, nervousness, and confusion.

The following adverse reactions have been reported in postmarketing experience with cyclobenzaprine ER products or cyclobenzaprine IR products, in clinical studies of cyclobenzaprine IR products (incidence <1%), or in postmarketing experience with other TCAs:

Body as a Whole: Syncope; malaise; chest pain; edema.

Cardiovascular: Tachycardia; arrhythmia; vasodilatation; palpitation; hypotension; hypertension; myocardial infarction; heart block; stroke.

Digestive: Vomiting; anorexia; diarrhea; gastrointestinal pain; gastritis; thirst; flatulence; edema of the tongue; abnormal liver function and rare reports of hepatitis, jaundice, and cholestasis; paralytic ileus, tongue discoloration; stomatitis; parotid swelling.

Endocrine: Inappropriate ADH syndrome.

Hematologic and Lymphatic: Purpura; bone marrow depression; leukopenia; eosinophilia; thrombocytopenia.

Hypersensitivity: Anaphylaxis; angioedema; pruritus; facial edema; urticaria; rash.

Metabolic, Nutritional, and Immune: Elevation and lowering of blood sugar levels; weight gain or loss.

Musculoskeletal: Local weakness; myalgia.

Nervous System and Psychiatric: Seizures, ataxia; vertigo; dysarthria; tremors; hypertonia; convulsions; muscle twitching; disorientation; insomnia; depressed mood; abnormal sensations; anxiety; agitation; psychosis, abnormal thinking and dreaming; hallucinations; excitement; paresthesia; diplopia; serotonin syndrome; neuroleptic malignant syndrome; decreased or increased libido; abnormal gait; delusions; aggressive behavior; paranoia; peripheral neuropathy; Bell's palsy; alteration in EEG patterns; extrapyramidal symptoms.

Respiratory: Dyspnea.

Skin: Sweating; photosensitization; alopecia.

Special Senses: Ageusia; tinnitus.

Urogenital: Urinary frequency and/or retention; impaired urination; dilatation of urinary tract; impotence; testicular swelling; gynecomastia; breast enlargement; galactorrhea.

7 DRUG INTERACTIONS

Based on its structural similarity to TCAs, concomitant use of TONMYA with:

- MAO inhibitors may be life-threatening [see Contraindications (4)],
- Alcohol, barbiturates, and other CNS depressants may increase the risk of adverse reactions associated with these drugs,
- Tramadol may increase the seizure risk,
- Guanethidine or other similar acting drugs may block the antihypertensive action of these drugs.

Postmarketing cases of serotonin syndrome have been reported with the concomitant use of oral cyclobenzaprine and other drugs, such as SSRIs, SNRIs, TCAs, tramadol, bupropion, meperidine, verapamil, or MAO inhibitors [see Warnings and Precautions (5.2)].

- The concomitant use of TONMYA with MAO inhibitors is contraindicated. If serotonin syndrome symptoms occur with the use of other serotonergic drugs, immediately discontinue TONMYA.
- If concomitant treatment with TONMYA and other serotonergic drugs (besides MAO inhibitors) is clinically warranted, careful observation is advised, particularly during dosage increases.

8 USE IN SPECIFIC POPULATIONS

8.1 Pregnancy

Risk Summary

Based on animal data, TONMYA may cause fetal harm when administered to a pregnant woman. In rabbits, an increased incidence of neural tube defects (splayed vertebral arches and spina bifida occulta) was observed when pregnant rabbits were treated with oral cyclobenzaprine during embryogenesis with 30 mg/kg/day (approximately 0.2 times the maximum recommended human dose (MRHD) of TONMYA), in the absence of maternal toxicity. In rats, decreased pup body weight and survival were noted at a cyclobenzaprine dose of ≥10 mg/kg/day (approximately ≥0.8 times the MRHD of TONMYA), when administered orally during pregnancy and lactation (see Data). The limited amount of available observational data on oral cyclobenzaprine use in pregnancy is of insufficient quality to inform a TONMYA-associated risk of major birth defects, miscarriage, or adverse maternal or fetal outcomes. Advise pregnant women about the potential risk to the fetus with maternal exposure to TONMYA and to avoid use of TONMYA two weeks prior to conception and through the first trimester of pregnancy.

The background risk of major birth defects and miscarriage for pregnant women with fibromyalgia is unknown. All pregnancies have a background risk of birth defect, loss, or other adverse outcomes. In the U.S. general population, the estimated background risk of major birth defects and miscarriage in clinically recognized pregnancies is 2% to 4% and 15% to 20%, respectively.

Report Pregnancies to the Tonix Medicines, Inc., Adverse Event reporting line at 1-888-869-7633 (1-888-TNXPMED).

Data

Animal Data:

Oral administration of cyclobenzaprine during organogenesis to rabbits at the highest maternal dose of 30 mg/kg/day (approximately 0.2 times the MRHD of 5.6 mg/day of TONMYA on an AUC basis) increased the incidence of neural tube defects (splayed vertebral arches and spina bifida occulta) in the absence of maternal toxicity. The no effect level for embryo-fetal development in rabbits was 10 mg/kg/day (approximately 0.05 times the MRHD of TONMYA on an AUC basis).

In another study, no adverse embryofetal effects were reported following oral administration of cyclobenzaprine during organogenesis to rabbits at maternal doses up to 20 mg/kg/day (approximately 0.1 times the MRHD of TONMYA on an estimated AUC basis).

No adverse embryofetal effects were reported following oral administration of cyclobenzaprine during organogenesis to rats at doses up to 25 mg/kg/day (approximately 9.2 times the MRHD of TONMYA, on an AUC basis). Maternal toxicity characterized by decreased body weight gain was observed in rats at this dose of 25 mg/kg/day.

No adverse embryofetal effects were reported following oral administration of cyclobenzaprine during organogenesis to mice at maternal doses up to 20 mg/kg/day (approximately 17 times the MRHD of TONMYA on a mg/m^2 basis). Maternal toxicity characterized by decreased body weight gain was observed at the highest tested dose of 20 mg/kg/day.

Decreased pup body weight and survival were reported in a prenatal and postnatal study where pregnant rats were treated orally with cyclobenzaprine during pregnancy and lactation with maternal doses of 10 and 20 mg/kg/day (approximately 0.8 and 1.7 times the MRHD of TONMYA on an estimated AUC basis). Maternal toxicity, characterized by a decreased body weight gain, was observed only at the highest tested dose of 20 mg/kg/day.

In another prenatal and postnatal study where pregnant rats were treated orally with cyclobenzaprine during pregnancy and lactation with maternal doses up to 10 mg/kg/day (approximately 0.8 times the MRHD of TONMYA on an AUC basis) no adverse effects were reported in maternal animals and offspring.

8.2 Lactation

Risk Summary

A small number of published cases report the transfer of cyclobenzaprine into human milk in low amounts, but these data cannot be confirmed. There are no data on the effects of cyclobenzaprine on a breastfed infant, or the effects on milk production. The developmental and health benefits of breastfeeding should be considered along with the mother's clinical need for TONMYA and any potential adverse effects on the breastfed child from TONMYA or from the underlying maternal condition.

8.3 Females and Males of Reproductive Potential

Based on animal data, TONMYA may cause neural tube defects at clinically relevant doses. Females of reproductive potential should avoid use of TONMYA two weeks prior to conception through the first trimester of pregnancy [see Use in Specific Populations (8.1)].

Pregnancy Testing

Pregnancy testing is recommended for females of reproductive potential prior to initiation of treatment with TONMYA.

Contraception

Females

Advise female patients of reproductive potential to use effective contraception during treatment with TONMYA and for two weeks after the final dose.

8.4 Pediatric Use

The safety and effectiveness of TONMYA have not been established in pediatric patients.

8.5 Geriatric Use

Of the total number of TONMYA-treated patients in the clinical trials in adult patients with fibromyalgia (Trials 1, 2, and 3) [see Clinical Studies (14)], none were 65 years of age and older. Clinical trials of TONMYA did not include sufficient numbers of patients 65 years of age and older to determine whether they respond differently from younger adult patients.

After administration of cyclobenzaprine extended release capsules, the plasma concentration and half-life of cyclobenzaprine were substantially increased in the subjects 65 years of age and older compared to those under 65 years of age [see Clinical Pharmacology (12.3)]. Given the higher cyclobenzaprine exposure in patients 65 years of age and older, the recommended TONMYA dosage in patients 65 years of age and older is 2.8 mg once daily at bedtime, lower than the recommended dosage in younger adult patients [see Dosage and Administration (2.2)].

8.6 Hepatic Impairment

The recommended dosage of TONMYA in patients with mild hepatic impairment (HI) (Child Pugh A) is 2.8 mg once daily at bedtime, lower than the recommended dosage in patients with normal hepatic function [see Dosage and Administration (2.2)]. The use of TONMYA is not recommended in patients with moderate HI (Child Pugh B) or severe HI (Child Pugh C).

Cyclobenzaprine exposure (AUC) was increased in patients with mild HI and moderate HI compared to subjects with normal hepatic function [see Clinical Pharmacology (12.3)], which may increase the risk of TONMYA-associated adverse reactions.

9 DRUG ABUSE AND DEPENDENCE

9.1 Controlled Substance

TONMYA contains cyclobenzaprine, which is not a controlled substance.

9.3 Dependence

Given the pharmacologic similarities among the TCAs, consider withdrawal symptoms when stopping TONMYA. Abrupt cessation of TONMYA treatment after prolonged administration may produce nausea, headache, and malaise. These are not indicative of addiction.

10 OVERDOSAGE

Overdose Signs, Symptoms, and Complications of Cyclobenzaprine Overdose

- The most common adverse reactions associated with cyclobenzaprine overdose are drowsiness and tachycardia.
- Less frequent overdose manifestations include tremor, agitation, coma, ataxia, hypertension, slurred speech, confusion, dizziness, nausea, vomiting, and hallucinations.
- Rare but potentially critical overdose manifestations that have been reported are cardiac arrest, chest pain, cardiac dysrhythmias, severe hypotension, seizures, cases of neuroleptic malignant syndrome and rhabdomyolysis, and death.

Changes in the electrocardiogram, particularly in QRS axis or width, are clinically significant indicators of cyclobenzaprine toxicity. Other potential cyclobenzaprine overdosage adverse reactions include any of the adverse reactions listed under Adverse Reactions (6).

Multiple drug ingestion (including alcohol) is common in deliberate cyclobenzaprine overdose.

Treatment of Cyclobenzaprine Overdose

Consider contacting the Poison Help line (1-800-222-1222) or a medical toxicologist for additional overdose management recommendations.

Signs and symptoms of toxicity may develop rapidly after cyclobenzaprine overdose; therefore, hospital monitoring is recommended as soon as possible. To reduce the risk of rare but potentially critical cyclobenzaprine overdose manifestations, obtain an ECG and immediately initiate cardiac monitoring. Protect the patient's airway and establish an intravenous line. Recommend observation with cardiac monitoring and observation for signs of CNS or respiratory depression, hypotension, cardiac dysrhythmias and/or conduction blocks, and seizures.

Monitoring of plasma cyclobenzaprine levels should not guide overdose management of the patient. Dialysis is probably of no value because of low plasma concentrations of cyclobenzaprine.

Treatment of Cardiovascular Overdosage Complications: A maximal limb-lead QRS duration of 0.1 seconds may be the best indication of the severity of the cyclobenzaprine overdose.

Serum alkalinization, to a pH of 7.45 to 7.55, using intravenous sodium bicarbonate and hyperventilation (as needed), should be instituted for patients with dysrhythmias and/or QRS widening. A pH >7.6 or a pCO2 <20 mmHg is undesirable. Dysrhythmias unresponsive to sodium bicarbonate therapy/hyperventilation may respond to lidocaine or phenytoin. Type 1A and 1C antiarrhythmics (e.g., quinidine, disopyramide, and procainamide) are generally contraindicated in the setting of a cyclobenzaprine overdose.

Treatment of CNS Overdosage Complications: In patients with CNS depression associated with a cyclobenzaprine overdose, early intubation is advised because of the potential for abrupt deterioration. Seizures should be controlled with benzodiazepines or, if these are ineffective, other anticonvulsants (e.g., phenobarbital, phenytoin). Physostigmine is not recommended except to treat life-threatening symptoms that have been unresponsive to other therapies, and then only in close consultation with a poison center.

11 DESCRIPTION

Cyclobenzaprine hydrochloride, USP is a white to off-white crystalline tricyclic amine salt powder, 1-Propanamine, 3-(5H-dibenzo[a,d] cyclohepten-5-ylidene)-N,N-dimethyl-, hydrochloride. The molecular formula is C20H21N ∙ HCl and the molecular weight is 311.85 g/mol, and it has a pK of 6.8. It is freely soluble in water and pH independent. Cyclobenzaprine hydrochloride has the following chemical structure:

Each sublingual tablet contains 2.8 mg of cyclobenzaprine hydrochloride (equivalent to 2.47 mg cyclobenzaprine) and the following inactive ingredients: colloidal silicon dioxide, corn starch, crospovidone (Type A), D&C Yellow No.10, dibasic potassium phosphate, mannitol, and sodium stearyl fumarate.

12 CLINICAL PHARMACOLOGY

12.1 Mechanism of Action

The mechanism of action of cyclobenzaprine for the treatment of fibromyalgia in adults is unknown. In in vitro pharmacology studies, cyclobenzaprine demonstrated functional antagonism of 5-HT2A, α1-adrenergic, H1-histaminergic, and M1-muscarinic acetylcholine receptors. In addition, pharmacological studies in animals demonstrated a similarity between the effects of cyclobenzaprine and the structurally related TCAs, including reserpine antagonism, norepinephrine potentiation, potent peripheral and central anticholinergic effects, and sedation.

12.2 Pharmacodynamics

The exposure-response relationship and time course of pharmacodynamic response for the safety and effectiveness of cyclobenzaprine have not been fully characterized.

12.3 Pharmacokinetics

Following single-dose sublingual administration of 2.8 mg and 5.6 mg of TONMYA in healthy adult subjects (n=16), Cmax, AUC0-tau, and AUC0-inf of cyclobenzaprine increased in an approximately dose-proportional manner.

In a multiple-dose study of 5.6 mg of TONMYA administered sublingually once daily for 20 days in healthy subjects (n=26), approximately 2.5-fold accumulation of plasma cyclobenzaprine exposure was observed at steady-state.

Absorption

The median time to peak plasma cyclobenzaprine concentration (Tmax) was approximately 4.3 hours for the 2.8 mg and 5.6 mg once daily TONMYA dosages.

Food Effect: A food effect study was conducted in healthy adult subjects (n=16) with a single sublingual 5.6 mg TONMYA dose. When TONMYA was administered with food, there was approximately 10% decrease in peak plasma concentration (Cmax) compared to the fasted state with no effect on exposure (AUC0-tau and AUC0-inf). These changes are not clinically significant.

Elimination

TONMYA has a single dose elimination half-life of approximately 36 hours (range 28-59 hours; n=16).

Metabolism: Cyclobenzaprine is extensively metabolized. Cytochromes P-450 3A4, 1A2, and, to a lesser extent, 2D6 mediate N-demethylation, one of the oxidative pathways for cyclobenzaprine metabolism.

Excretion: Cyclobenzaprine is excreted primarily as glucuronides via the kidney.

Specific Populations

Geriatric Patients: After cyclobenzaprine extended-release capsules dosing, the plasma cyclobenzaprine AUC was increased by 40% and the half-life of cyclobenzaprine was prolonged in geriatric subjects greater than 65 years of age compared to younger adult subjects 18 to 45 years of age (50 hours vs. 32 hours, respectively) [see Use in Specific Populations (8.5)]. There were no notable differences in Cmax or Tmax in this study.

Hepatic Impairment: In a pharmacokinetic study of immediate-release cyclobenzaprine tablets in 15 patients with mild hepatic impairment (HI) (Child-Pugh A) and 1 patient with moderate HI (Child-Pugh B), both AUC and Cmax were approximately double the values seen in subjects with normal hepatic function. The pharmacokinetics of cyclobenzaprine in patients with moderate HI (1 patient only) and severe HI is not known [see Use in Specific Populations (8.6)].

13 NONCLINICAL TOXICOLOGY

13.1 Carcinogenesis, Mutagenesis, Impairment of Fertility

Carcinogenesis

Long-term studies were conducted in CD-1 mice and Sprague-Dawley rats with oral cyclobenzaprine to evaluate its carcinogenic potential. In an 81-week carcinogenicity study, metastatic hemangiosarcoma was seen in 3 of 21 male mice at 10 mg/kg/day (approximately 9 times the maximum recommended human dose (MRHD) of 5.6 mg of TONMYA on a mg/m^2 basis). In a 105-week carcinogenicity study, malignant astrocytoma was seen in 3 of 50 male rats at 10 mg/kg/day (approximately 0.3 times the MRHD on an estimated AUC basis). There were no tumor findings in female mice or rats.

Mutagenesis

Cyclobenzaprine was not mutagenic or clastogenic in the following assays: in vitro Ames bacterial mutation assays, an in vitro Chinese hamster ovary (CHO) cell chromosomal aberration test, an in vitro CHO cell micronucleus test, and in vivo mouse bone marrow micronucleus assays.

Impairment of Fertility

Cyclobenzaprine HCl, when administered 70 and 14 days prior to mating to male and female rats, respectively, had no effects on fertility or reproductive performance at oral doses up to 20 mg/kg/day (approximately 1.1 and 3.8 times in males and females, respectively, the MRHD on an estimated AUC basis).

13.2 Animal Toxicology and/or Pharmacology

In a 67-week study with rats that received cyclobenzaprine at oral doses of 10, 20, or 40 mg/kg/day (approximately 0.3 to 4.3 times and 1.2 to 12.4 times in males and females, respectively, the maximum recommended human dose (MRHD) of 5.6 mg of TONMYA on an estimated AUC basis), there were findings in the liver consisting of midzonal vacuolation with lipidosis for males and midzonal and centrilobular hepatocytic enlargement for females. In addition, there were findings of centrilobular coagulative necrosis. In the higher dose groups, these microscopic changes were seen after 26 weeks and even earlier in rats that died prior to 26 weeks; at lower doses, these changes were not seen until after 26 weeks.

In a 26-week study with Cynomolgus monkeys that received cyclobenzaprine at oral of doses of 2.5, 5, 10, or 20 mg/kg/day, one monkey at 20 mg/kg/day (69 times the MRHD on mg/m^2 basis) was euthanized in week 17. Morbidity for this animal was attributed to findings of chronic pancreatitis, cholecystitis, cholangitis, and focal liver necrosis.

14 CLINICAL STUDIES

The efficacy of TONMYA for the treatment of fibromyalgia was assessed in three randomized, two-arm, parallel-group, double-blind, placebo-controlled multicenter trials (Trial 1 [NCT04172831], Trial 2 [NCT04508621], and Trial 3 [NCT05273749]). The trials enrolled 1,474 patients aged 18 to 65 (735 TONMYA-treated patients and 739 placebo-treated patients) who met the 2016 American College of Rheumatology (ACR) criteria for diagnosis of fibromyalgia (including generalized pain, defined as pain in at least 4 of 5 regions; symptoms that had been present at a similar level for at least 3 months; and widespread pain index (WPI) ≥7 and symptom severity scale (SSS) score ≥5, OR WPI between 4 to 6 and SSS scale score ≥9). In the trials, 95% of patients were female, 83% of patients were not Hispanic or Latino, and the percentage of White, Black, and Asian patients were 86%, 9%, and 1%, respectively. The mean age was 49 years (range 18 to 65 years), and the mean duration of fibromyalgia was 9 years (range 0 to 49 years).

Patients were randomized to receive bedtime sublingual treatment of either:

- 2.8 mg of TONMYA nightly for the first 2 weeks, and then 5.6 mg of TONMYA beginning on the evening of Day 15 through Week 14.
- Placebo administered through Week 14.

The primary endpoint in all three trials was the change from baseline to Week 14 in the weekly average of daily 24-hour recall pain intensity scores.

As measured by the 11-point (0-10) numeric rating scale (NRS), the minimum mean baseline pain score required for enrollment was 4. Within each trial, at baseline, the TONMYA and placebo groups had similar mean weekly averages of daily diary pain scores.

- In Trials 1 and 3, TONMYA demonstrated a statistically significant reduction in pain intensity scores as compared to placebo (Table 2).
- In Trial 2, there was no statistically significant treatment group difference (TONMYA minus placebo). Results of this trial may not have been generalizable due to the presence of factors outside the conduct of the study.

The least squares (LS) mean change from baseline in the weekly average of daily 24-hour recall pain intensity scores at Week 14 in adult patients with fibromyalgia for the TONMYA and placebo groups in Trial 1 and Trial 3 are presented in Table 2. The LS mean change from baseline in the weekly average of daily 24-hour recall pain intensity scores over the weeks of the study in adult patients with fibromyalgia in Trials 1 and 3 are presented in Figure 1.

Table 2: Primary Efficacy Endpoint: Mean Change from Baseline in Weekly Average of Daily 24-Hour Recall Pain Intensity Scores at Week 14 in Adult Patients with Fibromyalgia (Trials 1 and 3)
 | Placebo |  | TONMYA
Visit/ Statistics | Value | Change from baseline | Value | Change from baseline
Trial 1
Baseline
N | 255 |  | 248
Mean (SD) | 6.0 (1.08) |  | 6.1 (1.06)
(Minimum, Maximum) | (4, 9) |  | (4, 9)
Week 14
LS mean (SE) [LS means, differences and CIs were based on a mixed model for repeated measures with fixed, categorical effects of treatment, center, study week, and treatment-by-study week interaction, as well as the fixed covariates of baseline value and baseline value-by-study week interactions. An unstructured covariance matrix was used.] | 4.6 (0.12) | -1.5 (0.12) | 4.2 (0.12) | -1.9 (0.12)
95% CI | (4.3, 4.8) | (-1.7, -1.3) | (3.9, 4.4) | (-2.1, -1.7)
Difference in LS mean (SE) |  |  |  | -0.4 (0.16)
95% CI for difference in LS mean |  |  |  | (-0.7, -0.1)
p-value for difference |  |  |  | 0.010
Trial 3
Baseline
N | 225 |  | 231
Mean (SD) | 5.9 (1.08) |  | 5.9 (1.05)
(Minimum, Maximum) | (4, 9) |  | (4, 9)
Week 14
LS mean (SE) | 4.7 (0.12) | -1.2 (0.12) | 4.1 (0.12) | -1.8 (0.12)
95% CI | (4.5, 5.0) | (-1.4, -0.9) | (3.8, 4.3) | (-2.0, -1.6)
Difference in LS mean (SE) |  |  |  | -0.7 (0.16) [The difference in the LS mean (i.e., -0.7) was due to a rounding effect: the change from baseline was -1.82 in the TONMYA group and -1.16 in the placebo group, and the difference in LS mean between the groups was -0.66.]
95% CI for difference in LS mean |  |  |  | (-1.0, -0.3)
p-value for difference |  |  |  | <0.001
CI = confidence interval; LS = least squares; SD = standard deviation; SE = standard error

Figure 1 Mean Change from Baseline in Weekly Average of Daily 24-Hour Recall Pain Intensity Scores Over Time in Adult Patients with Fibromyalgia (Trials 1 and 3)

Trial 1

Error bars represent +/- the standard error (SE).

Trial 3

Error bars represent +/- the standard error (SE).

Figure 2 shows the percentage of patients in Trials 1 and 3 who achieved various degrees of improvement in the change from baseline to Week 14 in the weekly averages of daily diary pain scores. The figures are cumulative so that patients whose change from baseline is, for example, 50%, are also included at every level of improvement below 50%. Patients who did not complete the trial were assigned 0% improvement. For example, in Trial 1 and Trial 3, the percentage of TONMYA-treated patients who achieved at least a 30% improvement from baseline in their weekly average of daily 24-hour recall pain intensity score at Week 14 was 47% and 46%, respectively.

Figure 2 Patients Who Achieved Various Levels of Improvement in Pain Intensity at Week 14 – Trial 1 and Trial 3

Trial 1

Trial 3

16 HOW SUPPLIED/STORAGE AND HANDLING

16.1 How Supplied

TONMYA (cyclobenzaprine hydrochloride sublingual tablets) are supplied as 2.8 mg sublingual tablets and are round, yellow debossed "T" on one side and packaged in 30 cc high density polyethylene bottles with a 28 mm polypropylene child-resistant cap with induction seal. Each bottle contains polyester coil and a desiccant canister.

- 14 count bottle NDC [70792-102-14]
- 30 count bottle NDC [70792-102-30]
- 60 count bottle NDC [70792-102-60]
- 90 count bottle NDC [70792-102-90]

16.2 Storage and Handling

TONMYA (cyclobenzaprine hydrochloride sublingual tablets) are labeled for storage at USP controlled room temperature (20°C to 25°C [68°F to 77°F]) with excursions permitted between 15°C to 30°C (59°F to 86°F) [see USP Controlled Room Temperature].

Store and dispense in original container and protect from moisture. Remove the polyester coil on first use and discard. Keep the desiccant canister in the bottle for the entire period of use.

17 PATIENT COUNSELING INFORMATION

Advise the patient to read the FDA-approved patient labeling (Patient Information).

- Advise patients to not swallow whole, cut, crush, or chew TONMYA.
- Advise patients to moisten mouth with sips of water before administration of TONMYA to reduce the risk of oral numbness.
- Advise patients that if a dose is missed, take the next dose at the regularly scheduled time the following evening. Patients should not take two doses to make up for a missed dose.
- Advise patients to stop taking TONMYA and to notify their health care provider right away if they experience symptoms of an allergic reaction, such as difficulty breathing, hives, swelling of face or tongue, or itching.
- Advise patients that TONMYA should not be taken with MAO inhibitors or within 14 days after discontinuation of a MAO inhibitor.
- Caution patients about the risk of serotonin syndrome with concomitant use of TONMYA and other drugs, such as SSRIs, SNRIs, TCAs, tramadol, bupropion, meperidine, verapamil, or MAO inhibitors. Advise patients of the signs and symptoms of serotonin syndrome [see Warnings and Precautions (5.1)] and instruct patients to seek medical care immediately if they experience these symptoms.
- Advise patients to stop taking TONMYA and to notify their health care provider right away if they experience symptoms of arrhythmias or tachycardia.
- Advise patients that TONMYA may enhance the impairment effects of alcohol. These effects may also be seen if TONMYA is taken with other CNS depressants.
- Advise patients to report severe oral mucosal adverse reactions to their health care provider.
- Caution patients about operating a motor vehicle or hazardous machinery until it is reasonably certain that TONMYA therapy will not adversely affect their ability to engage in such activities.
- Advise patients to take TONMYA at approximately the same time each night.
- Inform female patients of reproductive potential that TONMYA may cause fetal harm and to inform their healthcare providers of a known or suspected pregnancy [see Use in Specific Populations (8.1)].
- Advise female patients of reproductive potential to use effective contraception during treatment with TONMYA and for two weeks after the final dose [see Use in Specific Populations (8.3)].
- Advise patients who are exposed to TONMYA during pregnancy to contact Tonix Medicines, Inc., at 1-888-869-7633 (1-888-TNXPMED).

Distributed by:
Tonix Medicines, Inc.
26 Main Street – Suite 101, Chatham, NJ 07928

Manufactured for:
Tonix Pharmaceuticals, Inc.
26 Main Street – Suite 101, Chatham, NJ 07928

Manufactured by:
Almac Pharma Services Limited
Craigavon, Northern Ireland BT63 5QD
United Kingdom
and
Almac Pharma Services LLC
2661 Audubon Rd
Audubon, PA 19403-2413, USA
and
Patheon Inc.
111 Consumers Drive
Whitby, Ontario L1N 5Z5, Canada

PATIENT INFORMATION
TONMYA™ (ton mye ah)
(cyclobenzaprine hydrochloride sublingual tablets)

What is TONMYA?
TONMYA is a prescription medicine used in adults for the treatment of fibromyalgia.
It is not known if TONMYA is safe and effective in children.

Do not use TONMYA if you:

- are allergic to cyclobenzaprine or any of the ingredients in TONMYA. See the end of the Patient Information leaflet for a complete list of ingredients in TONMYA.
  Stop taking TONMYA and call your healthcare provider or get medical help right away if you have symptoms of an allergic reaction such as:

- difficulty breathing
- hives

- swelling of your face or tongue
- itching

- are taking, or have stopped taking within the last 14 days, a medicine called monoamine oxidase (MAO) inhibitor. Ask your healthcare provider or pharmacist for a list of these medicines if you are not sure.
- have had a recent heart attack, have heart rhythm problems (arrhythmias) or heart failure
- have an overactive thyroid (hyperthyroidism)

Talk to your healthcare provider before taking this medicine if you have any of the conditions listed above.

Before taking TONMYA, tell your healthcare provider about all of your medical conditions, including if you:

- have a history of seizures
- have trouble emptying your bladder (urinary retention)
- have a history of eye problems including glaucoma
- have liver problems
- are pregnant or plan to become pregnant. TONMYA may harm your unborn baby. You should not take TONMYA if you are planning to become pregnant or during the first trimester (first 12 weeks) of pregnancy.
  Females who are able to become pregnant:
  - Your healthcare provider should do a pregnancy test before you start treatment with TONMYA.
  - Use effective birth control (contraception) during treatment with TONMYA and for 2 weeks after the final dose.
  - Tell your healthcare provider right away if you are planning to become pregnant, you become pregnant, or think you are pregnant during treatment with TONMYA.
  - If you are exposed to TONMYA during pregnancy, contact Tonix Medicine, Inc., at 1-888-869-7633 (1-888-TNXPMED).
- are breastfeeding or plan to breastfeed. TONMYA may pass into your breast milk. Talk to your healthcare provider about the best way to feed your baby during treatment with TONMYA.

Tell your healthcare provider about all the medicines you take, including prescription and over-the-counter medicines, vitamins, and herbal supplements.
Especially tell your healthcare provider if you take:

- a medicine to treat depression, mood, anxiety, psychotic, or thought disorders
- a pain medicine called tramadol or meperidine
- bupropion
- verapamil
- anticholinergic medicines
- barbiturates or other medicines that depress your central nervous system (CNS depressants)
- a blood pressure medicine called guanethidine

Ask your healthcare provider if you are not sure if you are taking any of these medicines. Your healthcare provider can tell you if it is safe to take TONMYA with your other medicines.
Know the medicines you take. Keep a list of your medicines with you and show it to your healthcare provider or pharmacist when you get a new medicine.

How should I take TONMYA?

- Take TONMYA exactly as your healthcare provider tells you to take it.
- Your healthcare provider will tell you how much TONMYA to take.
- Your healthcare provider may change your TONMYA dose if needed.
- Take TONMYA 1 time a day at bedtime, around the same time each evening.
- Take TONMYA after brushing your teeth and other oral care is completed.
- Your mouth and area under your tongue (sublingual) should be moist when you take TONMYA. Drink a few sips of water before you take TONMYA.
- Place the prescribed number of TONMYA sublingual tablet(s) under your tongue until it dissolves.
- Do not swallow whole, cut, crush, or chew TONMYA sublingual tablets.
- Avoid eating or drinking for at least 15 minutes after the TONMYA sublingual tablet is completely dissolved. Avoid any hot, cold, or acidic beverages until the morning.
- Avoid talking for at least 5 minutes after taking TONMYA.
- If you miss a dose of TONMYA, take your next dose the following evening. Do not take a missed dose during the day. Do not take 2 doses to make up for a missed dose.
- If you take too much TONMYA, call your healthcare provider or Poison Help line at 1-800-222-1222 or go to the nearest hospital emergency room right away.

What should I avoid while using TONMYA?

- You should not drink alcohol until you know how TONMYA affects you. Taking TONMYA with alcohol or other medicines that depress your central nervous system can slow your thinking and physical response times, and cause symptoms such as sleepiness.
- Do not drive, operate machinery, or do other dangerous activities until you know how TONMYA affects you.

What are possible side effects of TONMYA?
TONMYA may cause serious side effects, including:

- Serotonin syndrome. Serotonin syndrome is a serious condition that may be life-threatening and has happened when TONMYA is used with certain other medicines. Go to the nearest hospital emergency room right away if you develop any of following signs or symptoms of serotonin syndrome:
  - confusion, agitation, seeing or hearing things that are not real (hallucinations), coma, or other changes in mental status
  - high body temperature (hyperthermia)
  - shaking (tremor), coordination problems, or muscle twitching (overactive reflexes)
  - fast heartbeat, high or low blood pressure
  - sweating or fever
  - nausea, vomiting, or diarrhea
  - muscle stiffness or tightness
- TONMYA may cause serious side effects that may lead to heart attack or stroke. Stop taking TONMYA and go to the nearest hospital emergency room right away if you get:

- irregular or abnormal heartbeats (arrhythmias)
- fast heartbeat (tachycardia)
- dizziness

- lightheaded or feel faint
- chest pain or discomfort
- shortness of breath

- Side effects in your mouth. TONMYA can cause side effects to the lining inside your mouth, including numbness, tingling, discomfort, pain, irritation, swelling (inflammation), and sores (lesions). Side effects inside your mouth are common with TONMYA and can sometimes be severe. These side effects can happen within minutes of taking TONMYA, and most go away within 60 minutes. Drink a few sips of water before taking TONMYA to decrease your chance of getting numbness or reduced feeling in your mouth. Tell your healthcare provider right away if you have:
  - trouble eating, drinking, breathing, or swallowing
  - side effects that cover a large area in your mouth
  - pain in your mouth that makes it difficult to do your normal activities

The most common side effects of TONMYA include:

- reduced feeling in your mouth
- mouth discomfort
- abnormal TONMYA taste
- feeling sleepy (somnolence)
- numbness or tingling in your mouth

- mouth pain
- tiredness
- dry mouth
- sores in your mouth (canker sores)

These are not all the possible side effects of TONMYA.
Call your doctor for medical advice about side effects. You may report side effects to FDA at 1-800-FDA-1088.

How should I store TONMYA?

- Store TONMYA at room temperature between 68°F to 77°F (20°C to 25°C).
- Keep TONMYA in the original bottle. Protect from moisture.
- The TONMYA bottle contains a desiccant canister to help keep your medicine dry (protect it from moisture). Keep the desiccant canister in the bottle.
- The TONMYA bottle contains a polyester coil to help protect the sublingual tablets during shipping. Remove the polyester coil from the bottle and throw it away after opening the bottle for the first time.
- TONMYA comes in a child-resistant bottle.

Keep TONMYA and all medicines out of the reach of children.

General information about the safe and effective use of TONMYA.
Medicines are sometimes prescribed for purposes other than those listed in a Patient Information leaflet. Do not use TONMYA for a condition for which it was not prescribed. Do not give TONMYA to other people, even if they have the same symptoms you have. It may harm them. You can ask your pharmacist or healthcare provider for information about TONMYA that is written for health professionals.

What are the ingredients in TONMYA?
Active ingredient: cyclobenzaprine hydrochloride
Inactive ingredients: colloidal silicon dioxide, corn starch, crospovidone (Type A), D&C Yellow No.10, dibasic potassium phosphate, mannitol, and sodium stearyl fumarate.
Distributed by: Tonix Medicines, Inc., 26 Main Street – Suite 101, Chatham, NJ 07928
Manufactured for: Tonix Pharmaceuticals, Inc., 26 Main Street – Suite 101, Chatham, NJ 07928
Manufactured by: Almac Pharma Services Limited, Craigavon, Northern Ireland BT63 5QD, United Kingdom and Almac Pharma Services LLC, 2661 Audubon Rd, Audubon, PA 19403-2413, USA and Patheon Inc., 111 Consumers Drive, Whitby, Ontario L1N 5Z5, Canada
For optional information, visit www.TONMYA.com or call 1-888-869-7633 (1-888-TNXPMED).

This Patient Information has been approved by the U.S. Food and Drug Administration.

Issued MM/2025

PRINCIPAL DISPLAY PANEL - 2.8 mg Tablet Bottle Label

NDC 70792-102-30
30 Tablets

Rx ONLY

Tonmya™

(cyclobenzaprine HCl
sublingual tablets)

Distributed by:
Tonix Medicines, Inc.
Chatham, NJ 07928

2.8 mg

TONIX
MEDICINES